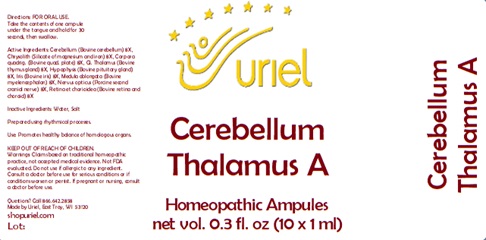 DRUG LABEL: Cerebellum Thalamus A
NDC: 48951-3048 | Form: LIQUID
Manufacturer: Uriel Pharmacy Inc.
Category: homeopathic | Type: HUMAN OTC DRUG LABEL
Date: 20241202

ACTIVE INGREDIENTS: BOS TAURUS CEREBELLUM 8 [hp_X]/1 mL; SILICON DIOXIDE 8 [hp_X]/1 mL; BOS TAURUS BRAIN 8 [hp_X]/1 mL; SUS SCROFA THALAMUS 8 [hp_X]/1 mL; BOS TAURUS PITUITARY GLAND 8 [hp_X]/1 mL; BOS TAURUS EYE 8 [hp_X]/1 mL; BOS TAURUS NERVE 8 [hp_X]/1 mL
INACTIVE INGREDIENTS: SODIUM CHLORIDE; WATER

Cerebellum Thalamus A

INDICATIONS AND USAGE

Directions: FOR ORAL USE.

DOSAGE AND ADMINISTRATION

Take the contents of one ampule under the tongue and hold for 30 seconds, then swallow.

ACTIVE INGREDIENT

Active Ingredients: Cerebellum (Bovine cerebellum) 8X, Chrysolith (Silicate of magnesium and iron) 8X, Corpora quadrig. (Bovine quad. plate) 8X, Gl. Thalamus (Bovine thymus gland) 8X, Hypophysis (Bovine pituitary gland) 8X, Iris (Bovine iris) 8X, Medula oblongata (Bovine myelencephalon) 8X, Nervus opticus (Porcine second cranial nerve) 8X, Retina et chorioidea (Bovine retina and choroid) 8X

Inactive Ingredients: Water, Salt

Prepared using rhythmical processes.

PURPOSE

Use: Promotes healthy balance of homologous organs.

KEEP OUT OF REACH OF CHILDREN.

WARNINGS

Warnings: Claims based on traditional homeopathic practice, not accepted medical evidence. Not FDA evaluated. Do not use if allergic to any ingredient. Consult a doctor before use for serious conditions or if conditions worsen or persist. If pregnant or nursing, consult a doctor before use.

QUESTIONS

Questions? Call 866.642.2858 Made by Uriel, East Troy, WI 53120 shopuriel.com Lot: